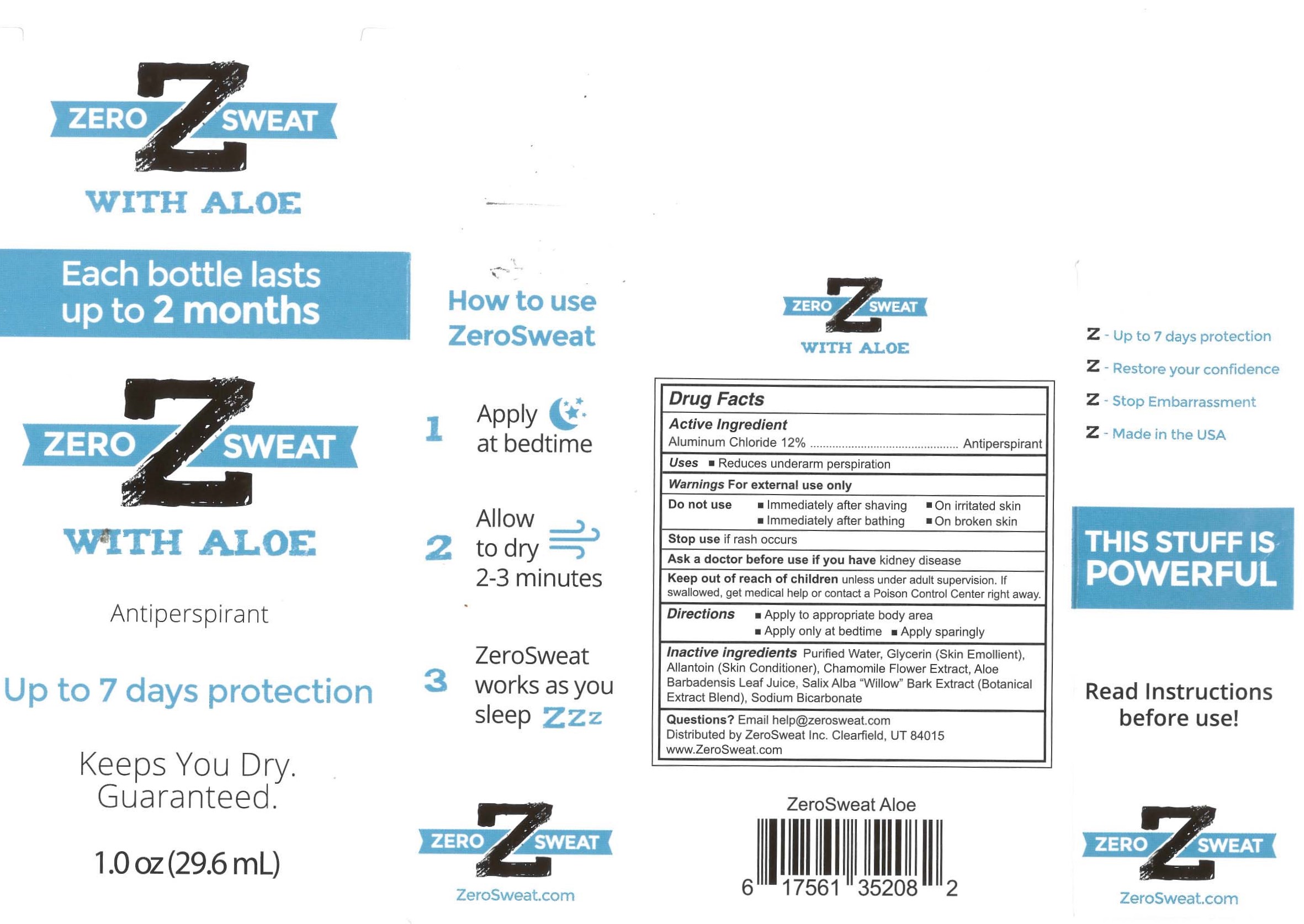 DRUG LABEL: ZeroSweat with Aloe
NDC: 65112-259 | Form: LIQUID
Manufacturer: I Shay Cosmetics Inc
Category: otc | Type: HUMAN OTC DRUG LABEL
Date: 20241113

ACTIVE INGREDIENTS: ALUMINUM CHLORIDE 0.12 g/1 g
INACTIVE INGREDIENTS: WATER 0.85 g/1 g; ALLANTOIN 0.005 g/1 g; GLYCERIN 0.02 g/1 g

ZeroSweat Antiperspirant 12%

ACTIVE INGREDIENT

Aluminum Chloride 12% ... Antiperspirant

PURPOSE

Antiperspirant

WARNING: Keep out of reach of children.

INDICATIONS AND USAGE

Reduces underarm perspiration.

INACTIVE INGREDIENT

Purified Water, Glycerin (Skin Emollient), Allantoin, Chamomile Flower Extract, Aloe Barbadensis Leaf Juice, Salix Alba “Willow” Bark Extract (Botanical Extract Blend), Sodium Bicarbonate.

WARNINGS

For external use only.

Do not use:

- Immediately after shaving
- Immediately after bathing
- On irritated skin
- On broken skin

Stop use if rash occurs
Ask a doctor before use if you have kidney disease

Keep out of reach of children unless under adult supervision. If swallowed, get medical help or contact a Poison Control Center right away.

DOSAGE AND ADMINISTRATION

Apply to the appropriate body area.

Apply only at bedtime

Apply sparingly